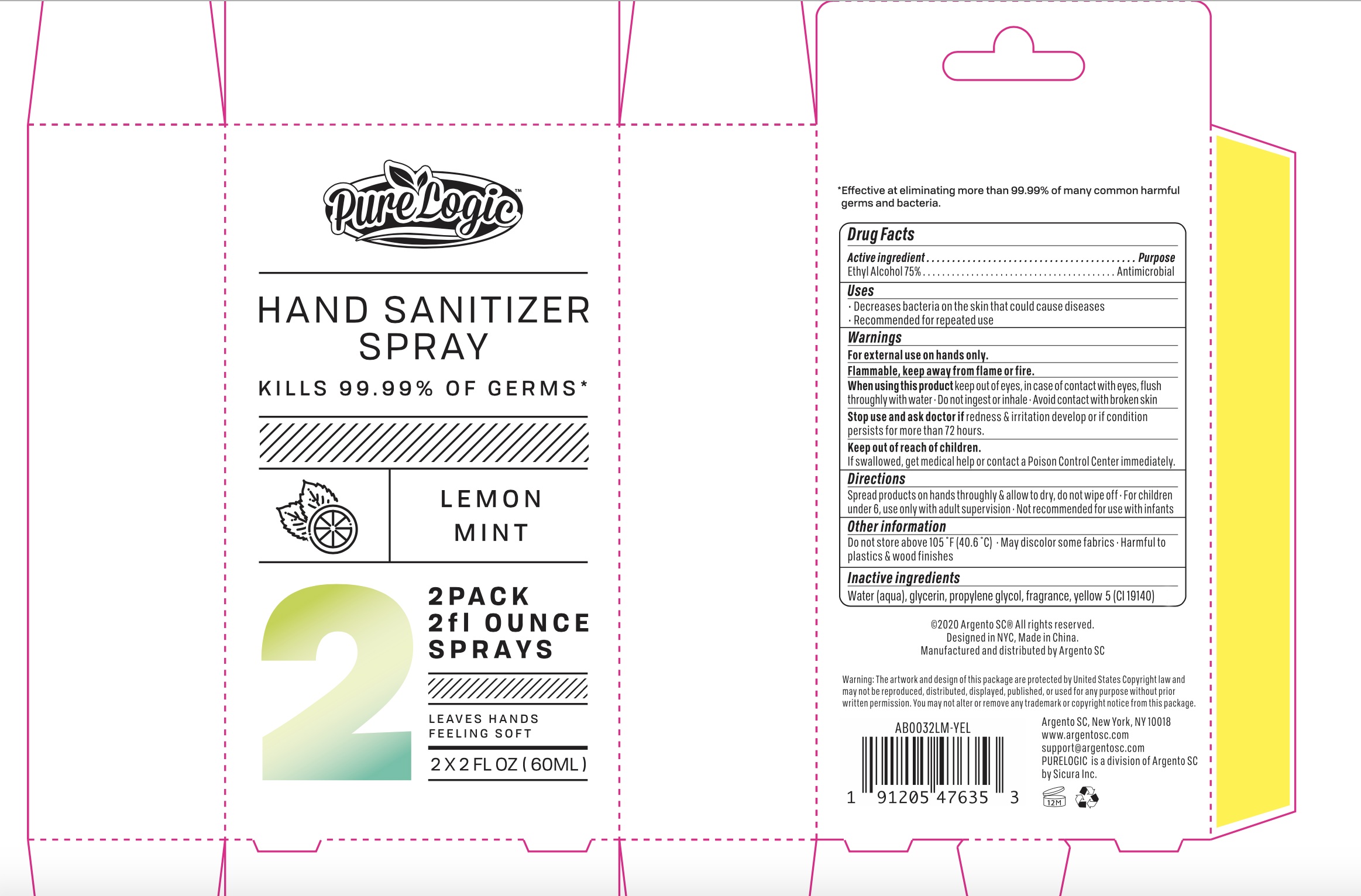 DRUG LABEL: PureLogic Hand Sanitizer Lemon Mint 2 Pack
NDC: 77731-049 | Form: SPRAY
Manufacturer: Argento sc by sicura inc.
Category: otc | Type: HUMAN OTC DRUG LABEL
Date: 20200801

ACTIVE INGREDIENTS: ALCOHOL 75 mL/100 mL
INACTIVE INGREDIENTS: GLYCERIN; PROPYLENE GLYCOL; WATER; FD&C YELLOW NO. 5

AB0032LM 2x 60 spray

Active Ingredient(s)

Ethyl Alcohol 75% v/v

Purpose:

Antimicrobial

Use

Decreases bacteria on skin that could cause diseases

Recommended for repeated use

Warnings

For external use on hands only. Flammable, keep way from flame or fire

When using this product, keep out of eyes. In case of contact with eyes, flush thoroughly with water

Do not ingest or inhale

Avoid contact with broken skin

Stop use and ask a doctor

if irrigation and redness develop or if condition persists for more than 72 hours

Keep out of reach of children

if swallowed,get medical help or contact a Poison Control Center immediately

Directions

- Spread product on hands thoroughly and allow to dry, do not wipe off
- For children under 6, use under adult supervision
- Not recommended for use with infants

Other information

Do not store above 105F (40.6C)

May discolor some fabrics

Harmful to plastics and wood finishes

Inactive ingredients

Purified water, Glycerin, Propylene Glycol, Fragrance, Yellow 5 (CI19140)